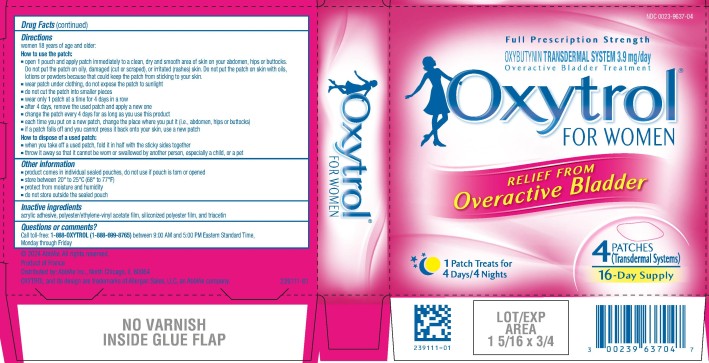 DRUG LABEL: Oxytrol for Women
NDC: 0023-9637 | Form: PATCH
Manufacturer: Allergan, Inc.
Category: otc | Type: HUMAN OTC DRUG LABEL
Date: 20240815

ACTIVE INGREDIENTS: OXYBUTYNIN 3.9 mg/1 d
INACTIVE INGREDIENTS: TRIACETIN

Drug Facts

Active ingredient (in each patch [transdermal system])

Oxybutynin 3.9 mg/day

Purpose

Overactive bladder treatment

Use

- treats overactive bladder in women
- you may be suffering from overactive bladder if you have had 2 or more of the following symptoms for at least 3 months:
  ○ urinary frequency (the need to urinate more often than usual; typically more than 8 times in 24 hours)
  ○ urinary urgency (a strong need to urinate right away)
  ○ urge incontinence (leaking or wetting yourself if you cannot control the urge to urinate)
- non-drug therapies may also help you (see the consumer information leaflet inside the package)

Warnings

For external use only

Frequent urination can also be caused by:

- urinary tract infections (UTI)
- diabetes
- early pregnancy
- other more serious conditions

If you think you might have one of these conditions, it is important to see your doctor before use.

Sleepiness, dizziness, confusion, and blurry vision may occur. Do not drive or operate machinery until you know how the patch affects you.

Do not use if you

- have any of these symptoms, which could be the sign of a UTI or other serious condition.
  See your doctor as soon as possible if you have:
  ○ pain or burning when urinating. These symptoms may also be accompanied by a fever or chills.
  ○ blood in your urine
  ○ unexplained lower back or side pain
  ○ urine that is cloudy, or foul-smelling
  ○ are male. Your symptoms may be due to a more serious condition.
  ○ are under the age of 18. It is not known if it works or is safe in children.
  ○ only experience accidental urine loss when you cough, sneeze or laugh, you may have stress incontinence. This product will not work for that condition.
  ○ have been told by a doctor you have urinary retention (are not able to empty your bladder)
  ○ have been told by a doctor you have gastric retention (your stomach empties slowly after a meal)
  ○ have glaucoma
  ○ are allergic to oxybutynin

Ask a doctor before use if you have

- symptoms of diabetes, such as:
  ○ excessive thirst
  ○ extreme hunger
- unexplained weight loss
- liver or kidney disease

Ask a doctor or pharmacist before use if you are

- taking a prescription medication for overactive bladder
- taking any drugs that may cause sleepiness, dizziness, dry mouth, constipation or blurred vision
- taking certain antibiotics (for example, erythromycin, clarithromycin) or prescription antifungals (for example, ketoconazole, itraconazole)

When using this product

- you may have itching, rash or redness where the patch was placed
- drinking alcohol may increase sleepiness

Stop use and ask a doctor if

- you are not able to empty your bladder (urinary retention)
- condition worsens, or if new symptoms appear
- condition does not improve after 2 weeks of use
- you have an allergic reaction to this product
- you have severe redness, itchiness or blistering at the site of application

Keep out of reach of children.

If swallowed, get medical help or contact a Poison Control Center right away.

Directions

women 18 years of age and older:

How to use the patch:

- open 1 pouch and apply patch immediately to a clean, dry and smooth area of skin on your abdomen, hips or buttocks. Do not put the patch on oily, damaged (cut or scraped), or irritated (rashes) skin. Do not put the patch on skin with oils, lotions or powders because that could keep the patch from sticking to your skin.
- wear patch under clothing, do not expose the patch to sunlight
- do not cut the patch into smaller pieces
- wear only 1 patch at a time for 4 days in a row
- after 4 days, remove the used patch and apply a new one
- change the patch every 4 days for as long as you use this product
- each time you put on a new patch, change the place where you put it (i.e., abdomen, hips or buttocks)
- if a patch falls off and you cannot press it back onto your skin, use a new patch

How to dispose of a used patch:

- when you take off a used patch, fold it in half with the sticky sides together
- throw it away so that it cannot be worn or swallowed by another person, especially a child, or a pet

Other information

- product comes in individual sealed pouches, do not use if pouch is torn or opened
- store between 20° to 25°C (68° to 77°F)
- protect from moisture and humidity
- do not store outside the sealed pouch

Inactive ingredients

acrylic adhesive, polyester/ethylene-vinyl acetate film, siliconized polyester film, and triacetin

Questions or comments?

Call toll-free: 1-888-OXYTROL (1-888-699-8765) between 9:00 AM and 5:00 PM Eastern Standard Time, Monday through Friday

© 2024 AbbVie. All rights reserved.

Made in USA

Distributed by: AbbVie Inc., North Chicago, IL 60064

OXYTROL and its design are trademarks of Allergan Sales, LLC, an AbbVie company.

PRINCIPAL DISPLAY PANEL

NDC 0023-9637-04
Full Prescription Strength
OXYBUTYNIN TRANSDERMAL SYSTEM 3.9 mg/day
Overactive Bladder Treatment
Oxytrol® FOR WOMEN
RELIEF FROM
Overactive Bladder
1 Patch Treats for
4 Days/4 Nights
4 PATCHES
(Transdermal Systems)
16-Day Supply